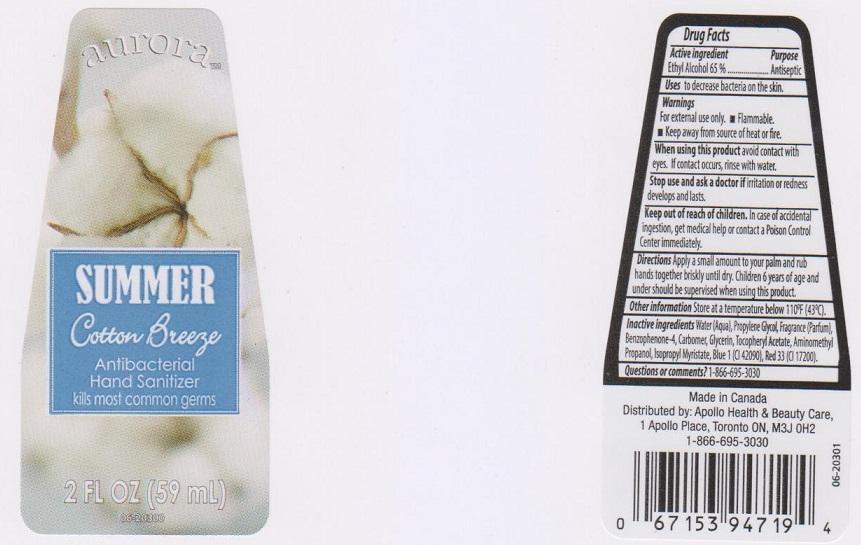 DRUG LABEL: AURORA
NDC: 63148-408 | Form: LIQUID
Manufacturer: APOLLO HEALTH AND BEAUTY CARE
Category: otc | Type: HUMAN OTC DRUG LABEL
Date: 20150114

ACTIVE INGREDIENTS: ALCOHOL 650 mg/1 mL
INACTIVE INGREDIENTS: WATER; PROPYLENE GLYCOL; SULISOBENZONE; CARBOMER 934; GLYCERIN; .ALPHA.-TOCOPHEROL ACETATE; AMINOMETHYLPROPANOL; ISOPROPYL MYRISTATE; FD&C BLUE NO. 1; D&C RED NO. 33

DRUG FACTS

ACTIVE INGREDIENT

ETHYL ALCOHOL 65%

PURPOSE

ANTISEPTIC

USES

TO DECREASE BACTERIA ON THE SKIN

WARNINGS

- FOR EXTERNAL USE ONLY
- FLAMMABLE
- KEEP AWAY FROM SOURCE OF HEAT OR FIRE

WHEN USING THIS PRODUCT

AVOID CONTACT WITH EYES. IF CONTACT OCCURS, RINSE WITH WATER

STOP USE AND ASK A DOCTOR IF

IRRITATION OR REDNESS DEVELOPS AND LASTS

KEEP OUT OF REACH OF CHILDREN

IN CASE OF ACCIDENTAL INGESTION, GET MEDICAL HELP OR CONTACT A POISON CONTROL CENTER IMMEDIATELY

DIRECTIONS

APPLY A SMALL AMOUNT TO YOUR PALM AND RUB HANDS TOGETHER BRISKLY UNTIL DRY. CHILDREN 6 YEARS OF AGE AND UNDER SHOULD BE SUPERVISED WHEN USING THIS PRODUCT

OTHER INFORMATION

STORE AT A TEMPERATURE BELOW 110°F (43°C)

INACTIVE INGREDIENTS

WATER (AQUA), PROPYLENE GLYCOL, FRAGRANCE (PARFUM), BENZOPHENONE-4, CARBOMER, GLYCEIRN, TOCOPHERYL ACETATE, AMINOMETHYL PROPANOL, ISOPROPYL MYRISTATE, BLUE 1 (CI 42090), RED 33 (CI 17200)

QUESTIONS OR COMMENTS?

1-866-695-3030